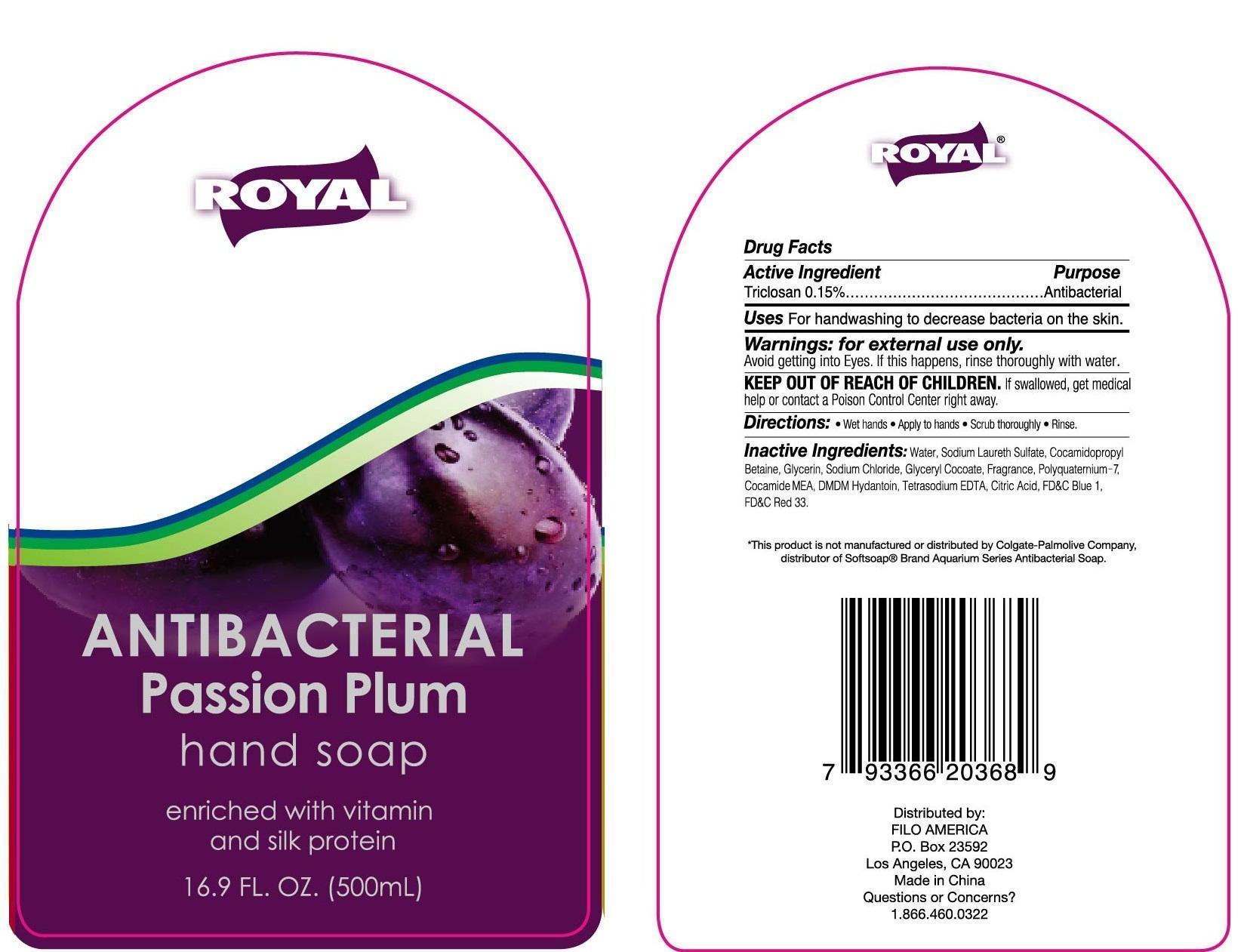 DRUG LABEL: Royal Antibacterial Passion Plum Hand Cleanse
NDC: 50438-107 | Form: GEL
Manufacturer: Filo America
Category: otc | Type: HUMAN OTC DRUG LABEL
Date: 20130917

ACTIVE INGREDIENTS: TRICLOSAN 1.5 mg/1 mL
INACTIVE INGREDIENTS: WATER; SODIUM C14-16 OLEFIN SULFONATE; SODIUM LAURETH SULFATE; COCO DIETHANOLAMIDE; SODIUM CHLORIDE; PEG-150 DISTEARATE; CITRIC ACID MONOHYDRATE; GLYCERIN; EDETATE DISODIUM; .ALPHA.-TOCOPHEROL ACETATE; METHYLCHLOROISOTHIAZOLINONE; FD&C YELLOW NO. 5; METHYLISOTHIAZOLINONE

Active Ingredient Purpose

Triclosan 0.15%..................................Antibacterial

Uses

for handwashing to decrease bacteria on the skin.

Keep out of reach of children. If swallowed, get medical help or contact a Poison Control Center right away.

INDICATIONS AND USAGE

Wet hand, apply to hands, scrub thoroughly, Rinse.

Warnings

For external use only.

Avoid getting into eyes. If this happens, rinse thoroughly with water.

DOSAGE AND ADMINISTRATION

Wet hand, apply palmful to hands, scrub thoroughly, Rinse.

Inactive Ingredients

camphor, carbomer, ethyl alcohol, fd&c blue no.1, isopropyl alcohol, methylchloroisothiazolinone, methylisothiazolinone, sodium hydroxide, water, cocamide MEA, PEG-18 glycaryl